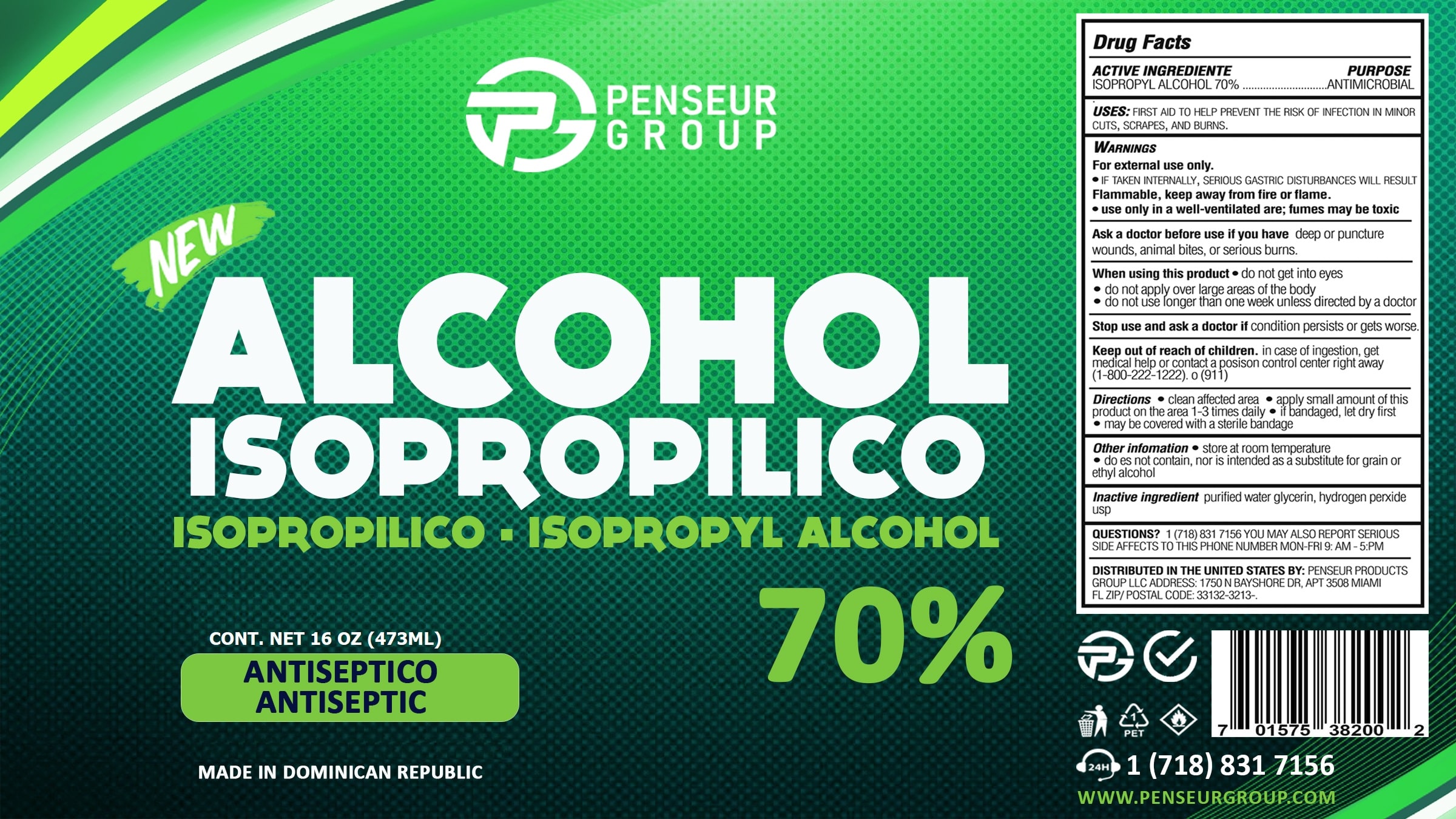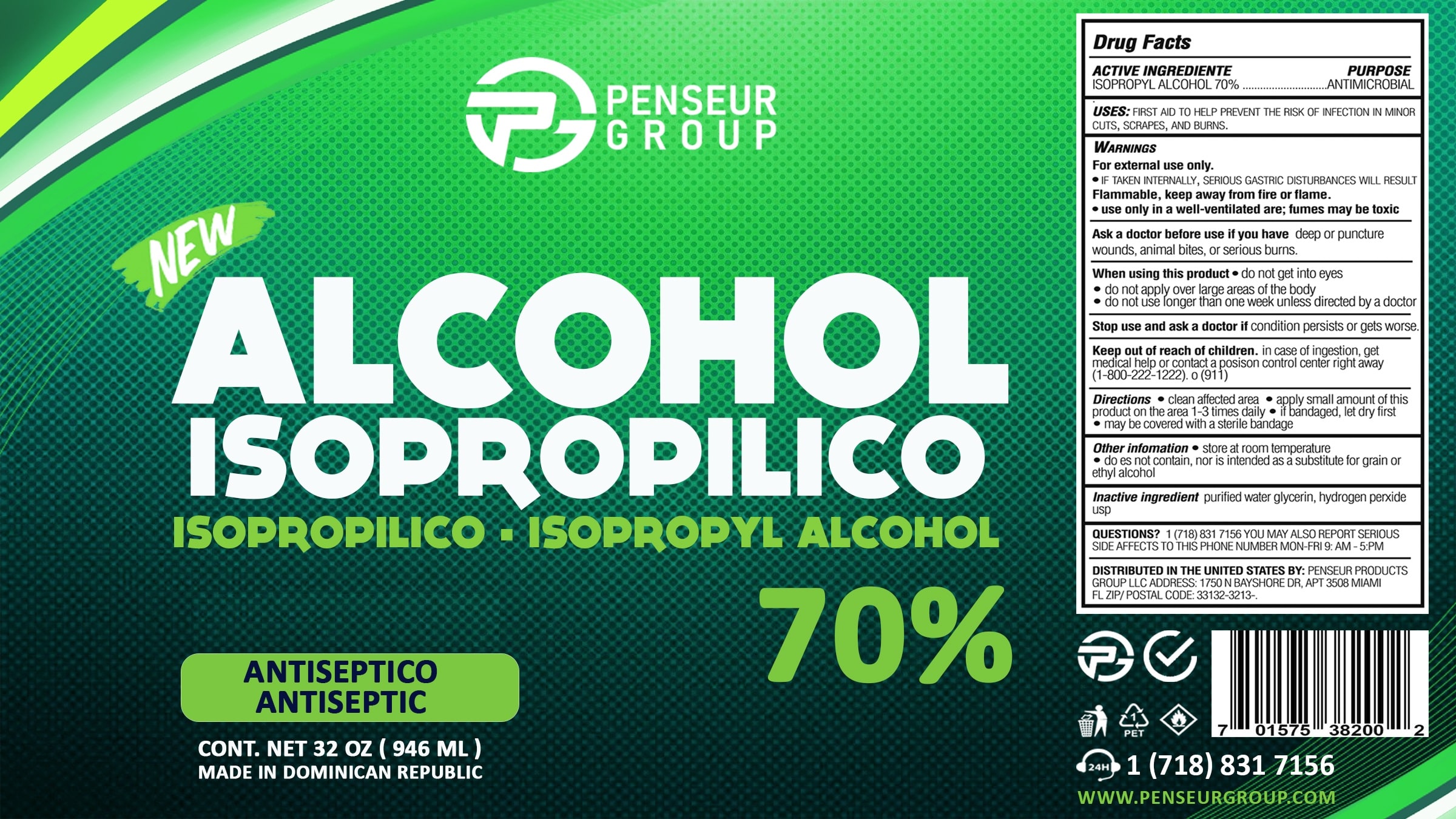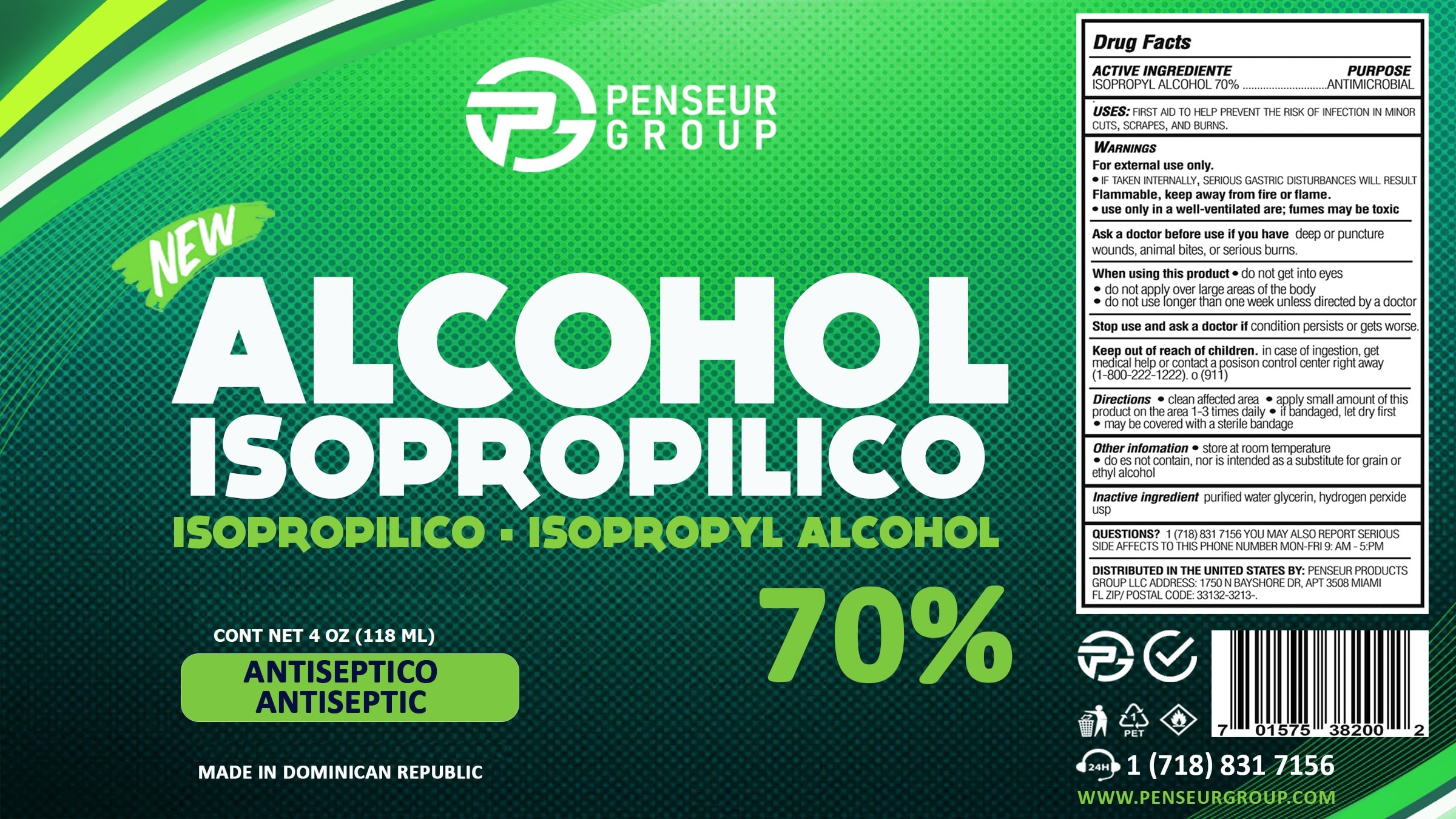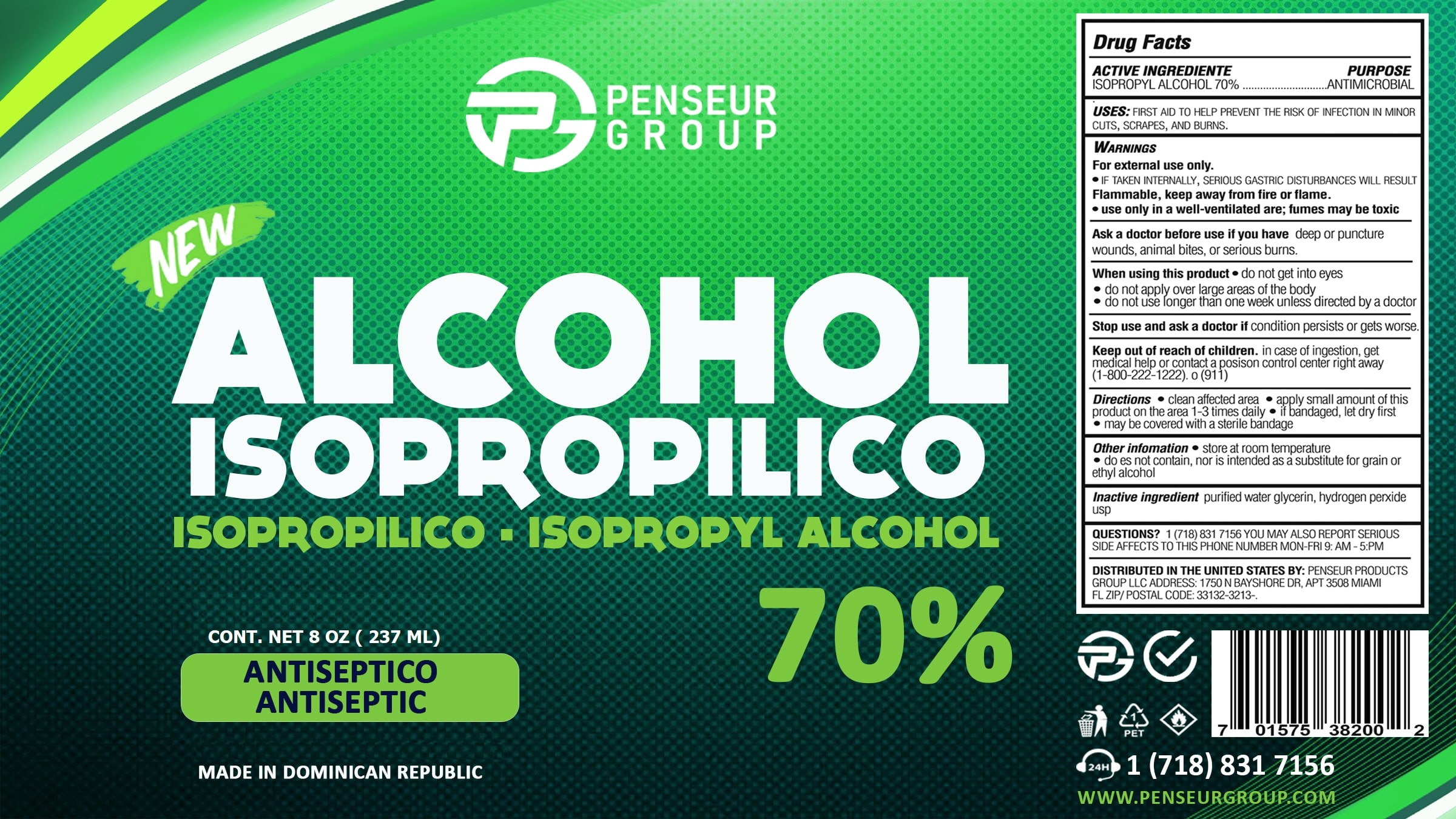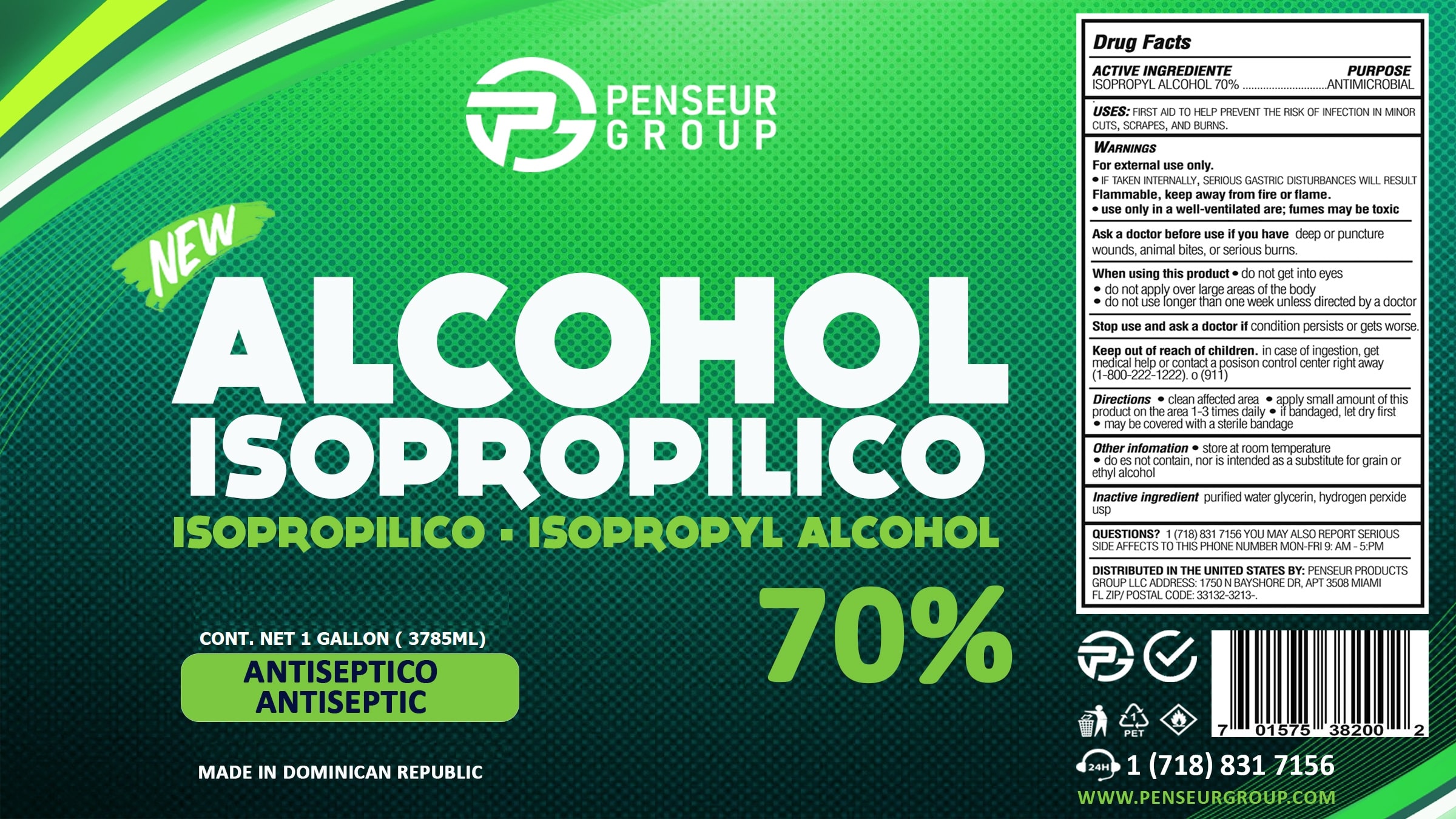 DRUG LABEL: Alcohol Isopropilico
NDC: 79878-004 | Form: LIQUID
Manufacturer: PENSEUR PRODUCTS GROUP LLC
Category: otc | Type: HUMAN OTC DRUG LABEL
Date: 20200823

ACTIVE INGREDIENTS: ISOPROPYL ALCOHOL 70 mL/100 mL
INACTIVE INGREDIENTS: GLYCERIN; HYDROGEN PEROXIDE; WATER

Active Ingredient(s)

Isopropyl Alcohol 70% v/v. Purpose: Antimicrobial

Purpose

Antimicrobial

Use

First aid to help prevent the risk of infection in minor cuts, scrapes, and burns.

Warnings

For external use only. Flammable. Keep away from heat or flame

Do not use

- if you have deep or puncture wounds, animal bites, or serious burns.

When using this product do not get into eyes. do not apply over large areas of the body. do not use longer than one week unless directed by a doctor.

Stop use and ask a doctor if condition persists or gets worse.
Keep out of reach of children. If swallowed, get medical help or contact a Poison Control Center right away.

Stop use and ask a doctor if irritation or rash occurs. These may be signs of a serious condition.

Keep out of reach of children. If swallowed, get medical help or contact a Poison Control Center right away.

Directions

- clean affected area
- apply small amount of this product on the area 1-3 times daily
- if bandaged, let dry first
- may be covered with a sterile bandage

Other information

- Store at room temperature
- Does not contain, nor is intended as a substitute for grain or ethyl alcohol

Inactive ingredients

glycerin, hydrogen peroxide, purified water USP

Package Label - Principal Display Panel

118 ml NDC: 79878-004-00

237 ml NDC: 79878-004-01

473 ml NDC: 79878-004-02

946 ml NDC: 79878-004-03

3785 ml NDC: 79878-004-04